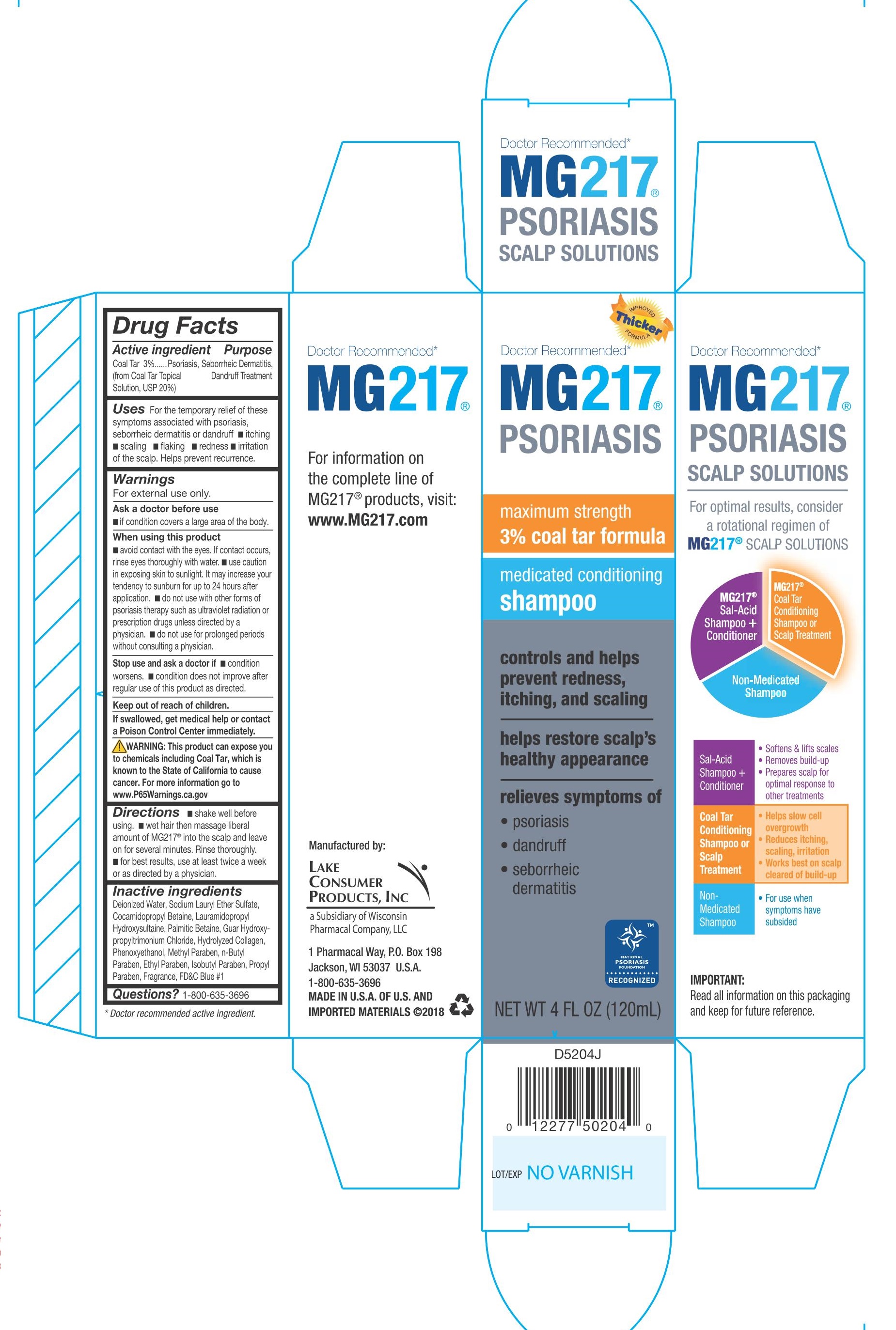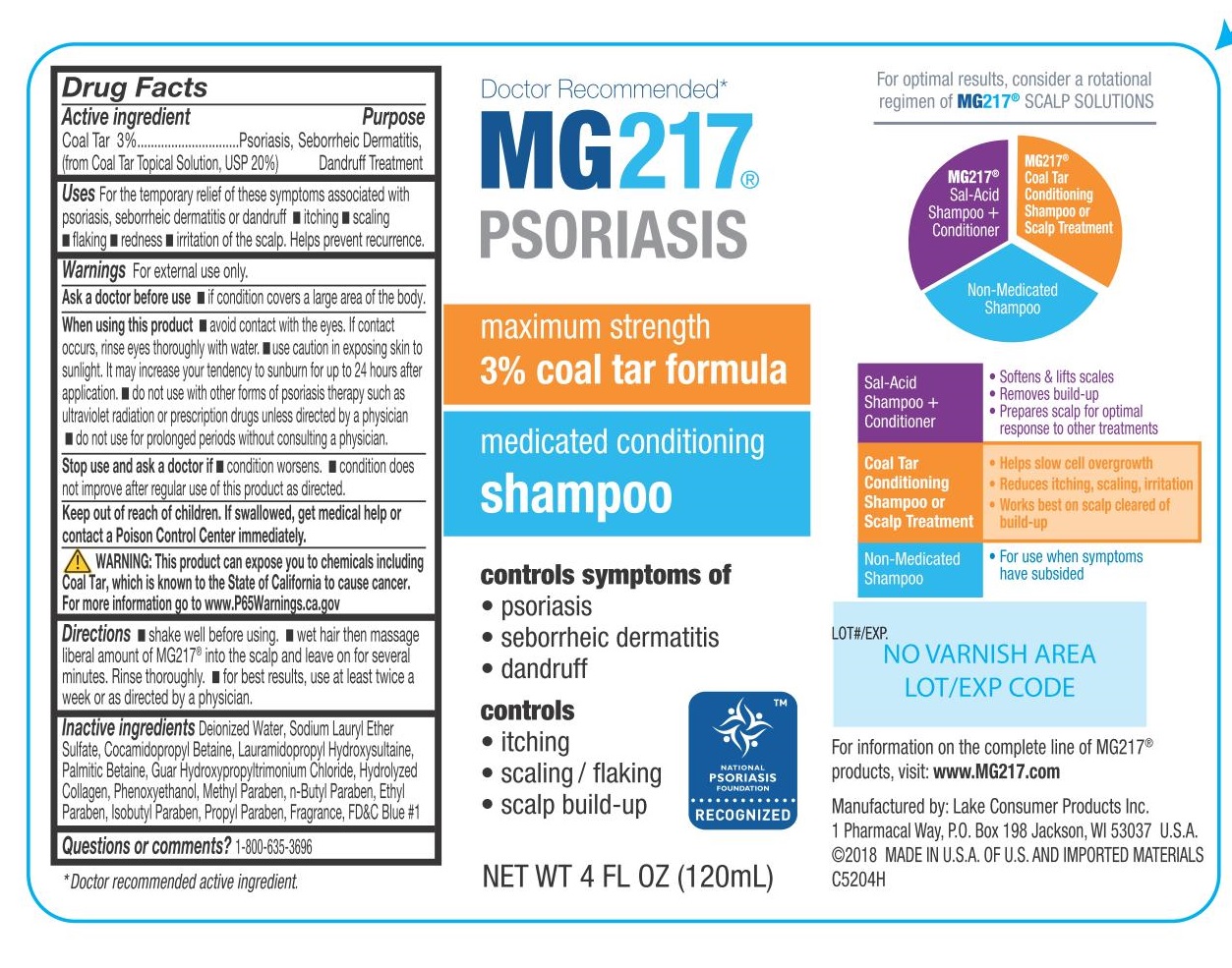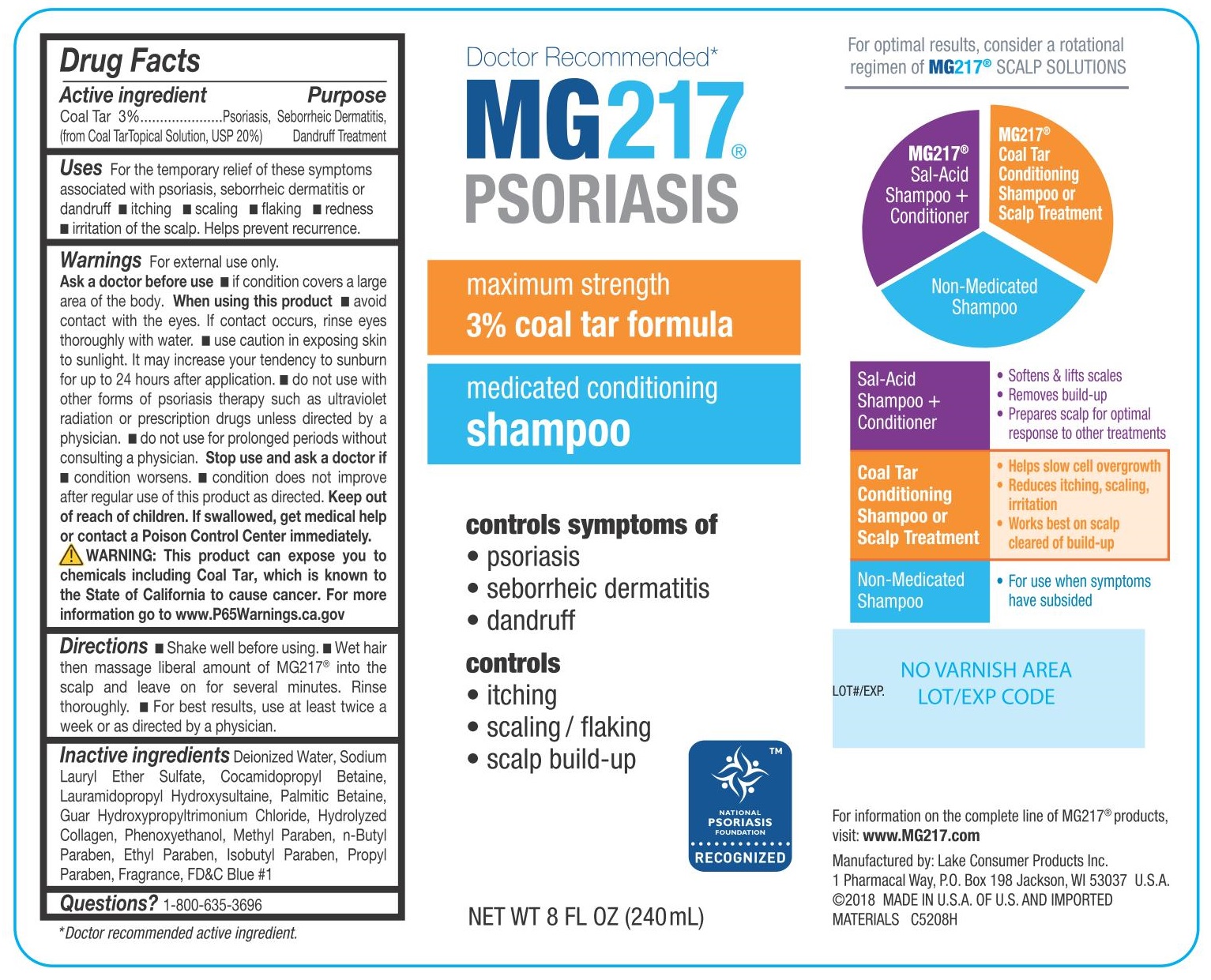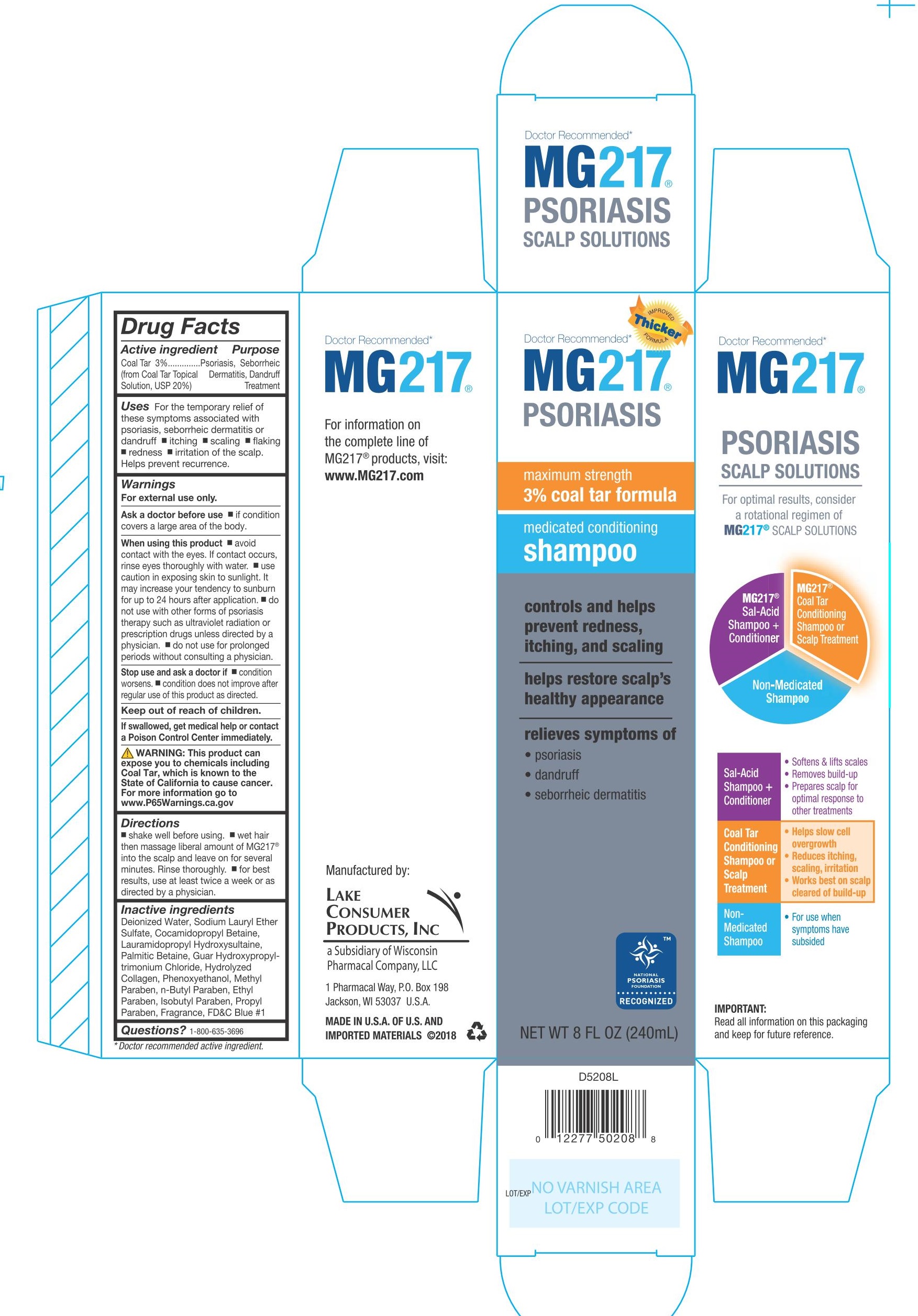 DRUG LABEL: MG217 Psoriasis
NDC: 68093-7232 | Form: SHAMPOO
Manufacturer: Wisconsin Pharmacal Company
Category: otc | Type: HUMAN OTC DRUG LABEL
Date: 20181210

ACTIVE INGREDIENTS: COAL TAR 0.03 g/1 g
INACTIVE INGREDIENTS: PORK COLLAGEN; ISOBUTYLPARABEN; WATER; COCAMIDOPROPYL BETAINE; GUAR GUM; METHYLPARABEN; SODIUM LAURETH SULFATE; BUTYLPARABEN; ETHYLPARABEN; LAURAMIDOPROPYL HYDROXYSULTAINE; PROPYLPARABEN; FD&C BLUE NO. 1; PHENOXYETHANOL; BETAINE

Active Ingredient

Coal Tar 3% (from Coal Tar Topical Solution, USP 20%)

Purpose

Psoriasis, Seborrheic Dermatitis, Dandruff Treatment

Uses

For the temporary relief of these symptoms associated with psoriasis, seborrheic dermatitis or dandruff

- itching
- scaling
- flaking
- redness
- irritation of the scalp.

Helps prevent recurrence.

Warnings

For external use only

Ask a doctor before use

- if condition covers a large area of the body.

When using this product

- avoid contact with the eyes. If contact occurs, rinse eyes thoroughly with water.
- use caution in exposing skin to sunlight. It may increase your tendency to sunburn for up to 24 hours after application.
- do not use with other forms of psoriasis therapy such as ultraviolet radiation or prescription drugs unless directed by a physician.
- do not use for prolonged periods without consulting a physician.

Stop use and ask a doctor if

- condition worsens.
- condition does not improve after regular use of this product as directed.

Keep out of reach of children.

OTHER SAFETY INFORMATION

If swallowed, get medical help or contact a Poison Control Center immediately.

WARNING: This product can expose you to chemicals including Coal Tar, which is known to the State of California to cause cancer. For more information go to www.P65Warnings.ca.gov

Directions

- shake well before using.
- wet hair then massage liberal amount of MG217 into the scalp and leave on for several minutes. Rinse thoroughly.
- for best results, use at least twice a week or as directed by a physician.

Inactive ingredients
Deionized Water, Sodium Lauryl Ether Sulfate, Cocamidopropyl Betaine, Lauramidopropyl Hydroxysultaine, Palmitic Betaine, Guar Hydroxypropyl-trimonium Chloride, Hydrolyzed Collagen, Phenoxyethanol, Methyl Paraben, n-Butyl Paraben, Ethyl Paraben, lsobutyl Paraben, Propyl Paraben, Fragrance, FD&C Blue #1

Questions? 1-800-635-3696